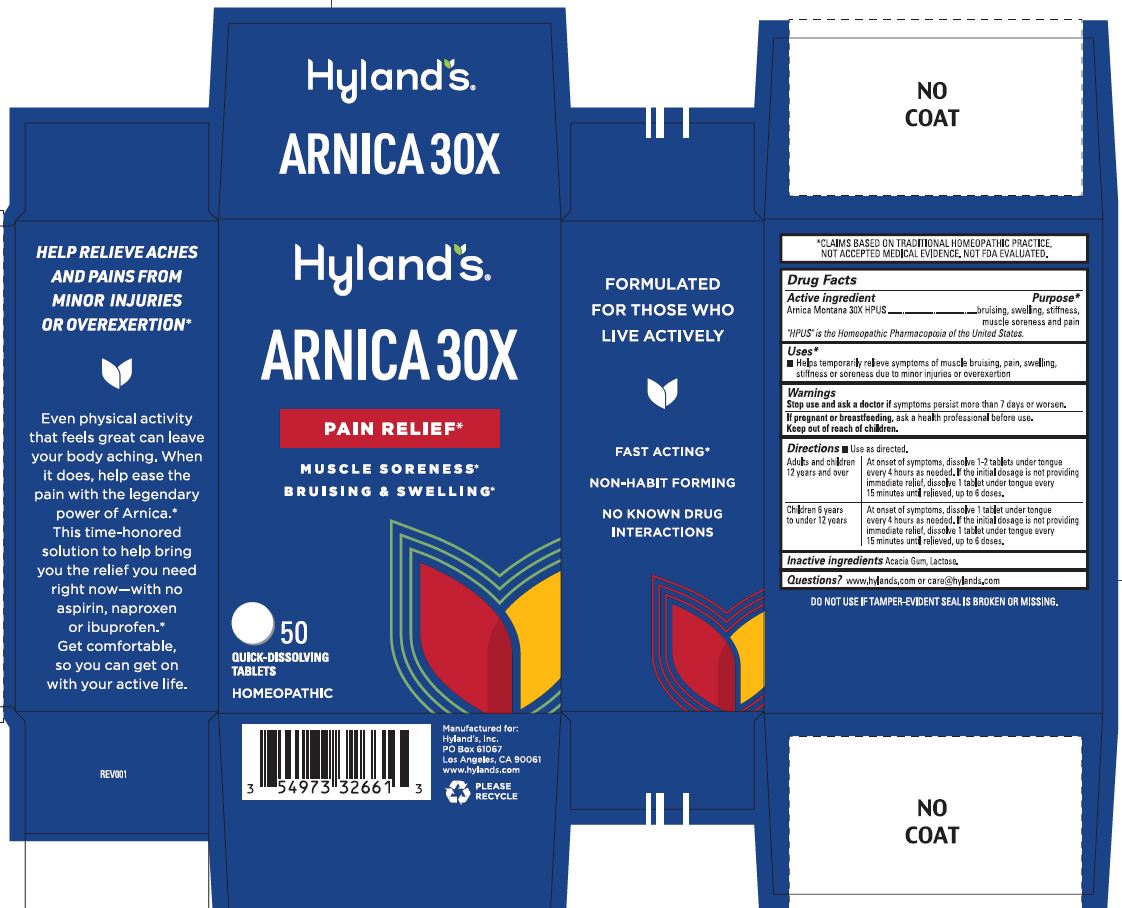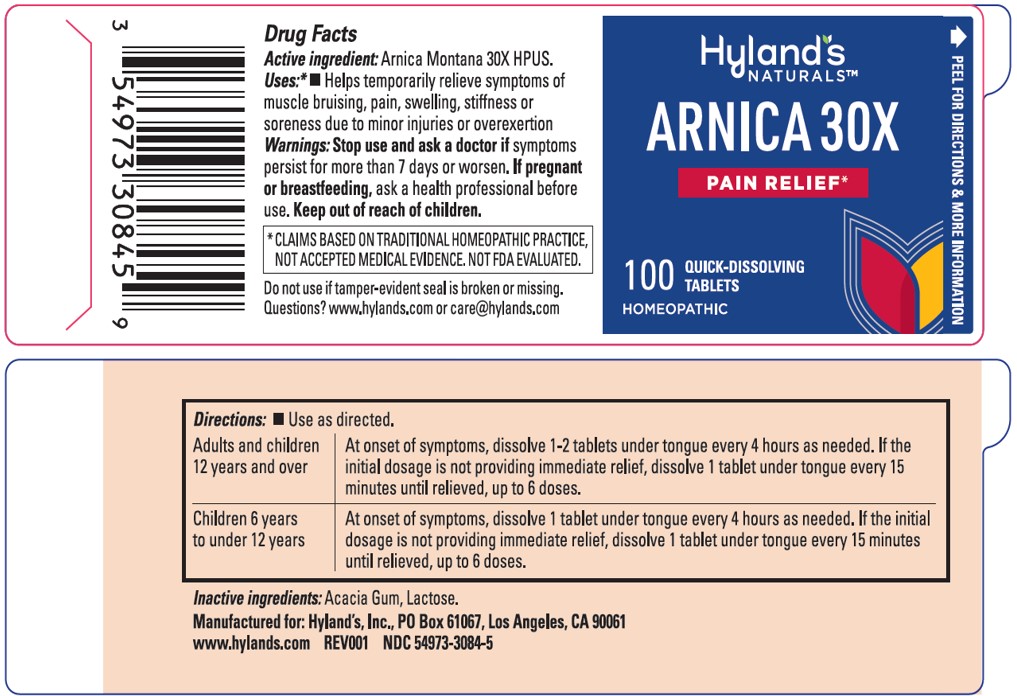 DRUG LABEL: ARNICA
NDC: 54973-3084 | Form: TABLET, SOLUBLE
Manufacturer: Hyland's Inc.
Category: homeopathic | Type: HUMAN OTC DRUG LABEL
Date: 20250410

ACTIVE INGREDIENTS: ARNICA MONTANA 30 [hp_X]/1 1
INACTIVE INGREDIENTS: LACTOSE; ACACIA

Hyland's Arnica 30X

Active ingredient | Purpose
Arnica Montana 30X HPUS | bruising, swelling, stiffness, muscle soreness and pain

Uses

■ Helps temporarily relieve symptoms of muscle bruising, pain, swelling, stiffness or soreness due to minor injuries or overexertion

Stop use and ask a doctor if symptoms persist more than 7 days or worsen.

PREGNANCY OR BREAST FEEDING

If pregnant or breastfeeding, ask a health professional before use.

Keep out of reach of children.

Directions

■ Use as directed.

Adults and children 12 years and over | At onset of symptoms, dissolve 1-2 tablets under tongue; every 4 hours as needed. If the initial dosage is not providing; immediate relief, dissolve 1 tablet under tongue every; 15 minutes until relieved, up to 6 doses.
Children 6 years to under 12 years | At onset of symptoms, dissolve 1 tablet under tongue every 4 hours as needed. If the initial dosage is not providing immediate relief, dissolve 1 tablet under tongue every 15 minutes until relieved, up to 6 doses.

Inactive ingredients

Acacia Gum, Lactose.

Questions?

www.hylands.com or care@hylands.com

*CLAIMS BASED ON TRADITIONAL HOMEOPATHIC PRACTICE, NOT ACCEPTED MEDICAL EVIDENCE. NOT FDA EVALUATED.

DO NOT USE IF TAMPER-EVIDENT SEAL IS BROKEN OR MISSING.

PURPOSE

Helps temporarily relieve symptoms of muscle bruising, pain, swelling, stiffness or soreness due to minor injuries or overexertion.